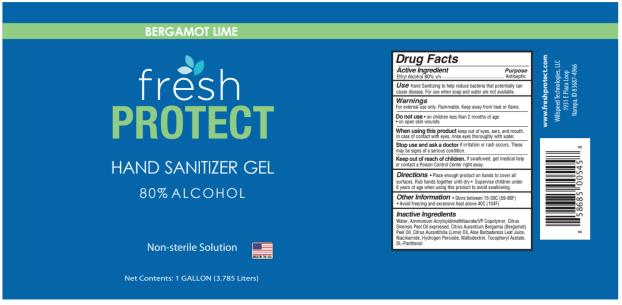 DRUG LABEL: Fresh Protect Hand Sanitizer
NDC: 69243-0110 | Form: GEL
Manufacturer: Willspeed Technologies LLC
Category: otc | Type: HUMAN OTC DRUG LABEL
Date: 20200818

ACTIVE INGREDIENTS: ALCOHOL 0.8 g/1 mL
INACTIVE INGREDIENTS: WATER; AMMONIUM ACRYLOYLDIMETHYLTAURATE/VP COPOLYMER; ORANGE OIL TERPENELESS; BERGAMOT OIL; LIME OIL; ALOE VERA LEAF; NIACINAMIDE; HYDROGEN PEROXIDE; MALTODEXTRIN; .ALPHA.-TOCOPHEROL ACETATE; PANTHENOL

Fresh Protect Gel Scented Pump

Fresh Protect Gel Scented

Drug Facts

Active Ingredients

Ethyl Alcohol 80% v/v

Purpose

Antimicrobial

Uses

- hand sanitizing to help reduce bacteria that potentially can cause disease. For use when soap and water are not available.

Warnings

For external use only. Do not drink.

Flammable. Keep away from heat and flame

Do not use

on children less than 2 years of age. - on open skin wounds

When using this product

keep out of eyes, ears, and mouth. In case of contact with eyes, rinse eyes thoroughly with water.

Stop use and ask a doctor

if irritation or rash occurs. These may be signs of a serious condition

Keep out of reach of children.

If swallowed, get medical help or contact a Poison Control Center right away.

Directions

- Place enough product on hands to cover all surfaces - supervised children under 6 years of age when using this product to avoid swallowing.

Other information

- store at 15C to 30C (59F to 86F) - Avoid freezing and excessive heat above 40C (104F)

Inactive Ingredients

Water, Ammonium Acryloyldimethltaurate/VP Copolymer, Citrus Sinensis Peel Oil expressed, Citrus Aurantium Bergamia (Bergamot Peel Oil, Citrus Aurantifolia (Lime) Oil, Aloe Barbadensis Leaf Juice, Niacinamide, Hydrogen Peroxide, Maltodextrin, Tocopheryl Acetate, DL-Panthenol

PRINCIPAL DISPLAY PANEL

Fresh
PROTECT
HAND SANITIZER GEL
80% ALCOHOL
Non-sterile solution